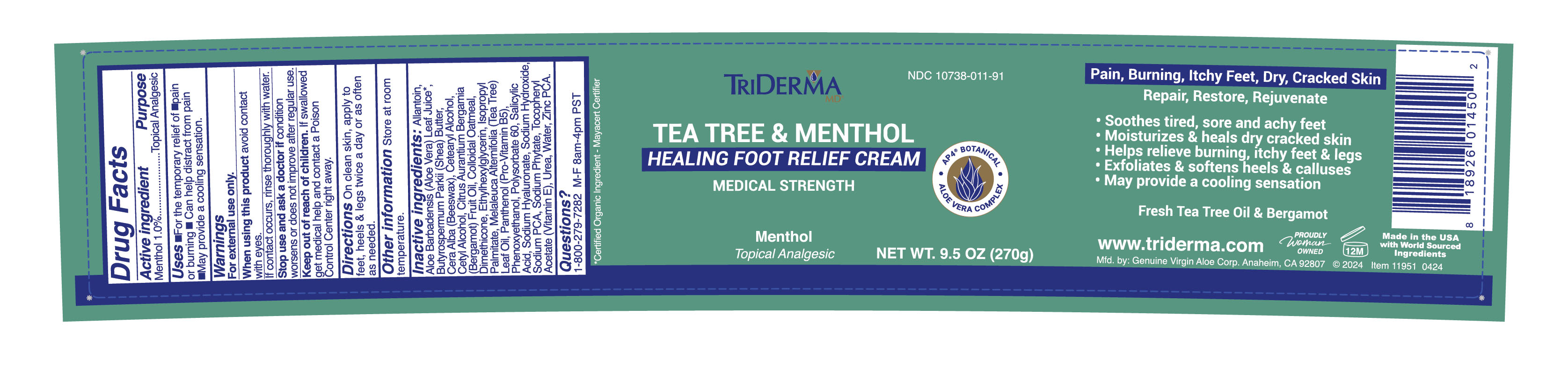 DRUG LABEL: TriDerma Tea Tree Foot Cream
NDC: 10738-011 | Form: CREAM
Manufacturer: Genuine Virgin Aloe Corporation
Category: otc | Type: HUMAN OTC DRUG LABEL
Date: 20260131

ACTIVE INGREDIENTS: MENTHOL 1 g/100 g
INACTIVE INGREDIENTS: DIMETHICONE 100; BEESWAX; ALOE VERA LEAF JUICE; SHEA BUTTER; ALLANTOIN; ARNICA MONTANA FLOWER; CETEARYL ALCOHOL; OATMEAL; CETYL ALCOHOL; SODIUM PCA; BERGAMOT OIL; TEA TREE OIL; SODIUM HYALURONATE

TriDerma Tea Tree Foot Cream

WARNINGS

For external use only

PURPOSE

Topical Analgesic

DIRECTIONS

On clean skin, apply to feet, heels and legs twice a day or as often as needed.

INACTIVE INGREDIENTS

Allantoin, Aloe Barbadensis Leaf Juice*, Butyrospermum Parkii (Shea) Butter, Cera Alba (Beeswax), Cetearyl Alcohol, Cetyl Alcohol, Citrus Aurantium Bergamia (Bergamot) Fruit Oil, Colloidal Oatmeal, Dimethicone, Ethylhexylglycerin, Isopropyl Palmitate, Melaleuca Alternifolia (Tea Tree) Leaf Oil, Panthenol (Pro-Vitamin B5), Phenoxyethanol, Polysorbate 60, Salicylic Acid, Sodium Hyaluronate, Sodium Hydroxide, Sodium PCA, Sodium Phytate, Tocopheryl Acetate (Vitamin E), Urea, Water, Zinc PCA.

*Certified Organic Ingredient - Mayacert Certifier

ACTIVE INGREDIENT

Menthol 1.0%

USES

for the temporary relief of pain and burning. Can help distract from pain. May provide a cooling sensation

WHEN USING THIS PRODUCT:

avoid contact with eyes

KEEP OUT OF REACH OF CHILDREN

if swallowed get medical help and contact a Poison Control Center right away.

STOP USE AND ASK A DOCTOR IF:

condition worsens or does not improve within 7 days.